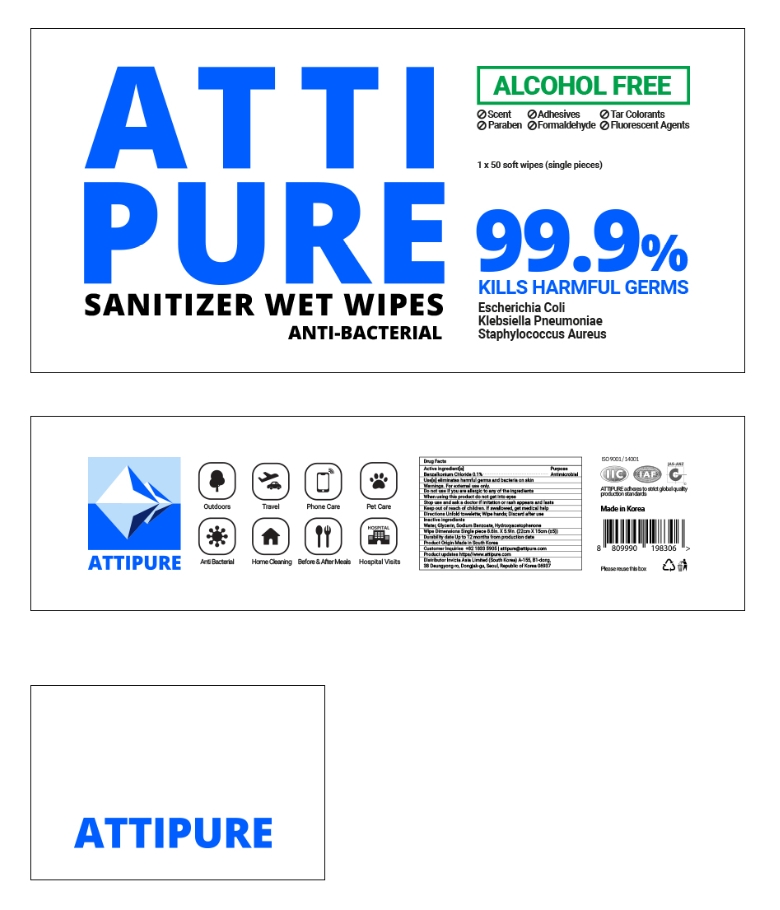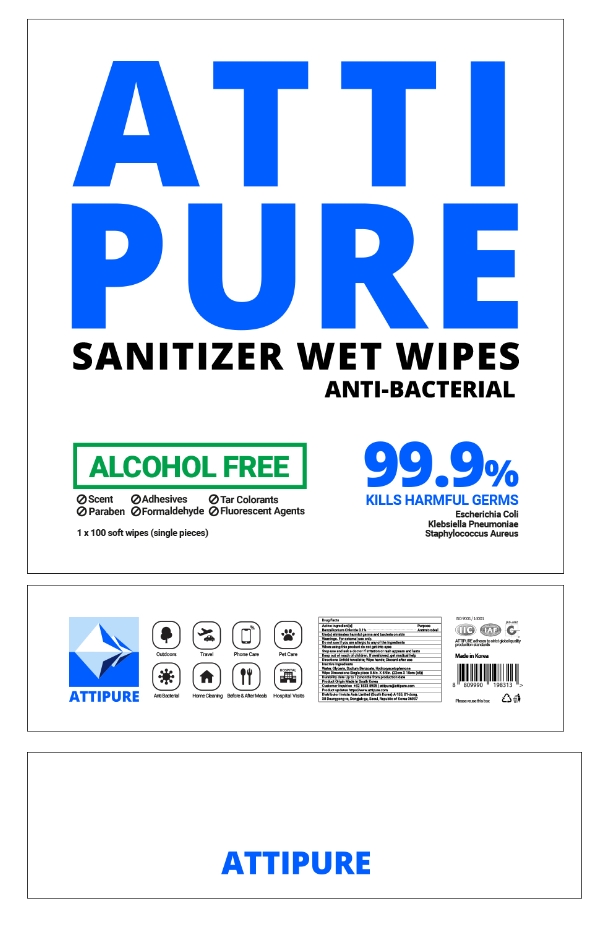 DRUG LABEL: ATTIPURE SANITIZER WET WIPES
NDC: 76709-201 | Form: LIQUID
Manufacturer: INVICTA ASIA CO., LTD
Category: otc | Type: HUMAN OTC DRUG LABEL
Date: 20200425

ACTIVE INGREDIENTS: BENZALKONIUM CHLORIDE 100 mg/100 g
INACTIVE INGREDIENTS: GLYCERIN; SODIUM BENZOATE; HYDROXYACETOPHENONE; WATER

Active ingredient[s]

Benzalkonium Chloride 0.1%

Purpose

Antimicrobial

Use[s]

eliminates harmful germs and bacteria on skin

Warnings.

For external use only.

Do not use

if you are allergic to any of the ingredients

When using this product

do not get into eyes

Stop use and ask a doctor

if irritation or rash appears and lasts

Keep out of reach of children.

If swallowed, get medical help

Directions

Unfold towelette; Wipe hands; Discard after use

Inactive ingredients

Water, Glycerin, Sodium Benzoate, Hydroxyacetophenone